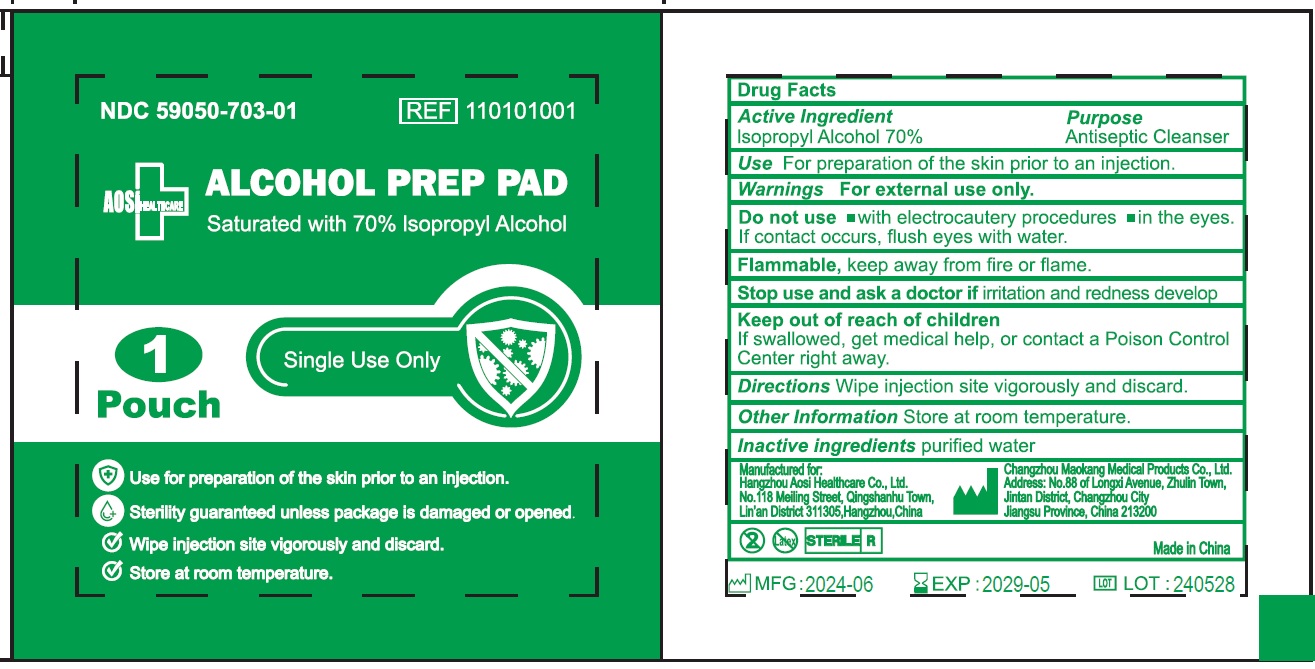 DRUG LABEL: Alcohol Prep Pad
NDC: 59050-703 | Form: LIQUID
Manufacturer: Changzhou Maokang Medical Products Co., Ltd
Category: otc | Type: HUMAN OTC DRUG LABEL
Date: 20241121

ACTIVE INGREDIENTS: ISOPROPYL ALCOHOL 0.7 mL/1 g
INACTIVE INGREDIENTS: WATER

Alcohol Prep Pad

Active Ingredient

Isopropyl Alcohol 70%

Purpose

Antiseptic Cleanser

Use

For preparation of the skin prior to an injection.

Warnings

For external use only.

Do not use

- with electrocautery procedures
- in the eyes. If contact occurs, flush eyes with water.

Flammable, keep away from fire or flame.

Stop use and ask a doctor if

irritation and redness develop

Keep out of reach of children

If swallowed, get medical help, or contact a Poison Control Center right away.

Directions

Wipe injection site vigorously and discard.

Other Information

Store at room temperature.

Inactive ingredients

purified water